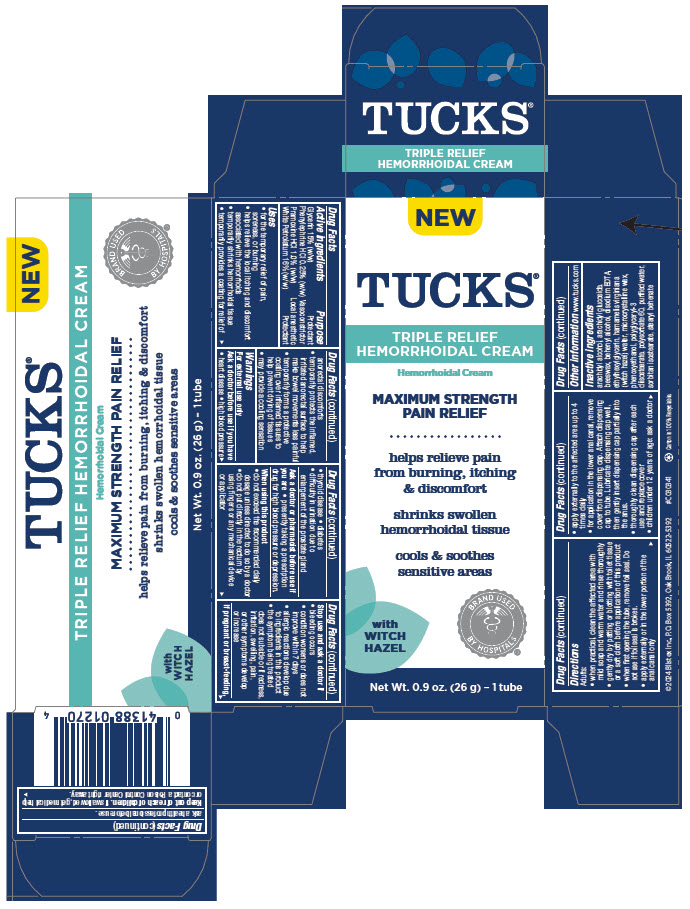 DRUG LABEL: Tucks Triple Relief Hemorrhoidal
NDC: 10157-2126 | Form: CREAM
Manufacturer: Blistex Inc.
Category: otc | Type: HUMAN OTC DRUG LABEL
Date: 20241224

ACTIVE INGREDIENTS: WHITE PETROLATUM 16 g/100 g; GLYCERIN 15 g/100 g; PRAMOXINE HYDROCHLORIDE 1 g/100 g; PHENYLEPHRINE HYDROCHLORIDE 0.25 g/100 g
INACTIVE INGREDIENTS: WATER; MICROCRYSTALLINE WAX; POLYSORBATE 60; STEARYL BEHENATE; SORBITAN ISOSTEARATE; HAMAMELIS VIRGINIANA TOP WATER; POLYGLYCERYL-3 DIISOSTEARATE; ARACHIDYL ALCOHOL; DOCOSANOL; ARACHIDYL GLUCOSIDE; YELLOW WAX; PHENOXYETHANOL; ETHYLHEXYLGLYCERIN; EDETATE DISODIUM

Tucks® Triple Relief Hemorrhoidal

Drug Facts

ACTIVE INGREDIENT

Active ingredients | Purpose
Glycerin 15% (w/w) | Protectant
Phenylephrine HCl 0.25% (w/w) | Vasoconstrictor
Pramoxine HCl 1.0% (w/w) | Local anesthetic
White Petrolatum 16% (w/w) | Protectant

Uses

- for the temporary relief of pain, soreness, or burning
- helps relieve the local itching and discomfort associated with hemorrhoids
- temporarily shrinks hemorrhoidal tissue
- temporarily provides a coating for relief of anorectal discomforts
- temporarily protects the inflamed, irritated anorectal surface to help make bowel movements less painful
- temporarily forms a protective coating over inflamed tissues to help prevent drying of tissues
- may provide a cooling sensation

Warnings

For external use only

Ask a doctor before use if you have

- heart disease
- high blood pressure
- thyroid disease
- diabetes
- difficulty in urination due to enlargement of the prostate gland

Ask a doctor or pharmacist before use if you are

- presently taking a prescription drug for high blood pressure or depression.

When using this product

- do not exceed the recommended daily dosage unless directed to do so by a doctor
- do not put directly in the rectum by using fingers or any mechanical device or applicator

Stop use and ask a doctor if

- bleeding occurs
- condition worsens or does not improve within 7 days
- allergic reactions develop due to ingredients in this product
- the symptom being treated does not subside or if redness, irritation, swelling, pain, or other symptoms develop or increase

PREGNANCY OR BREAST FEEDING

If pregnant or breast-feeding, ask a health professional before use.

Keep out of reach of children. If swallowed, get medical help or contact a Poison Control Center right away.

Directions

Adults:

- when practical, clean the affected area with mild soap and warm water and rinse thoroughly
- gently dry by patting or blotting with toilet tissue or a soft cloth before application of this product
- when first opening the tube, remove foil seal. Do not use if foil seal is broken.
- apply externally or in the lower portion of the anal canal only
- apply externally to the affected area up to 4 times daily
- for application in the lower anal canal, remove cover from dispensing cap. Attach dispensing cap to tube. Lubricate dispensing cap well, then gently insert dispensing cap partially into the anus.
- thoroughly clean dispensing cap after each use and replace cover
- children under 12 years of age: ask a doctor

Other information

www.tucks.com

Inactive ingredients

arachidyl alcohol, arachidyl glucoside, beeswax, behenyl alcohol, disodium EDTA, ethylhexylglycerin, hamamelis virginiana (witch hazel) water, microcrystalline wax, phenoxyethanol, polyglyceryl-3 diisostearate, polysorbate 60, purified water, sorbitan isostearate, stearyl behenate

PRINCIPAL DISPLAY PANEL - 26 g Tube Carton

NEW

TUCKS®

TRIPLE RELIEF
HEMORRHOIDAL CREAM

Hemorrhoidal Cream

MAXIMUM STRENGTH
PAIN RELIEF

helps relieve pain
from burning, itching
& discomfort

shrinks swollen
hemorrhoidal tissue

cools & soothes
sensitive areas

BRAND USED
BY HOSPITALS

with
WITCH
HAZEL

Net Wt. 0.9 oz. (26 g) - 1 tube